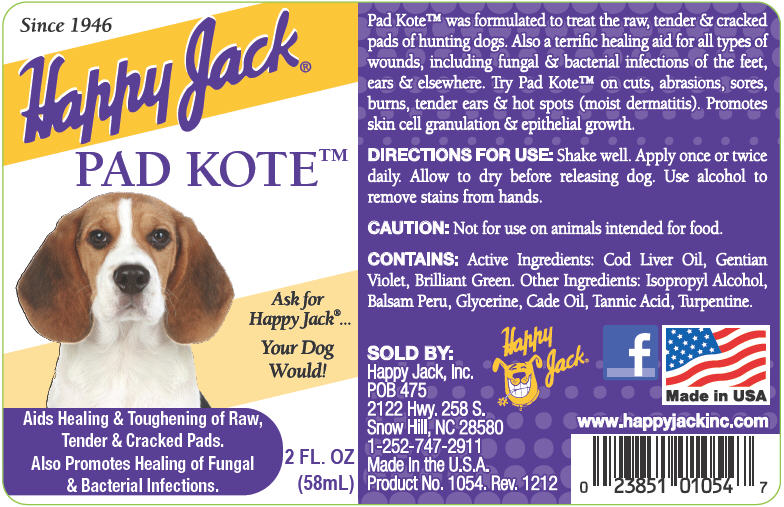 DRUG LABEL: Pad Kote
NDC: 23851-054 | Form: SUSPENSION
Manufacturer: Happy Jack Inc
Category: animal | Type: OTC ANIMAL DRUG LABEL
Date: 20240221

ACTIVE INGREDIENTS: cod liver oil 84 mg/1 mL; gentian violet 65 mg/1 mL; brilliant green 10 mg/1 mL
INACTIVE INGREDIENTS: isopropyl alcohol; balsam peru; glycerin; juniper tar; tannic acid; turpentine

Happy Jack®
PAD KOTE™

DESCRIPTION

Pad Kote™ was formulated to treat the raw, tender & cracked pads of hunting dogs. Also a terrific healing aid for all types of wounds, including fungal & bacterial infections of the feet, ears & elsewhere. Try Pad Kote™ on cuts, abrasions, sores, burns, tender ears & hot spots (moist dermatitis). Promotes skin cell granulation & epithelial growth.

DIRECTIONS FOR USE

Shake well. Apply once or twice daily. Allow to dry before releasing dog. Use alcohol to remove stains from hands.

CAUTION

Not for use on animals intended for food.

CONTAINS

Active Ingredients

Cod Liver Oil, Gentian Violet, Brilliant Green.

Other Ingredients

Isopropyl Alcohol, Balsam Peru, Glycerine, Cade Oil, Tannic Acid, Turpentine.

SOLD BY:
Happy Jack, Inc.
POB 475
2122 Hwy. 258 S.
Snow Hill, NC 28580
1-252-747-2911
Made in the U.S.A.
Product No. 1054. Rev. 1212

www.happyjackinc.com

PRINCIPAL DISPLAY PANEL - 58 mL Bottle Label

Since 1946

Happy Jack®

PAD KOTE™

Ask for
Happy Jack®...

Your Dog
Would!

Aids Healing & Toughening of Raw,
Tender & Cracked Pads.
Also Promotes Healing of Fungal
& Bacterial Infections.

2 FL. OZ
(58mL)